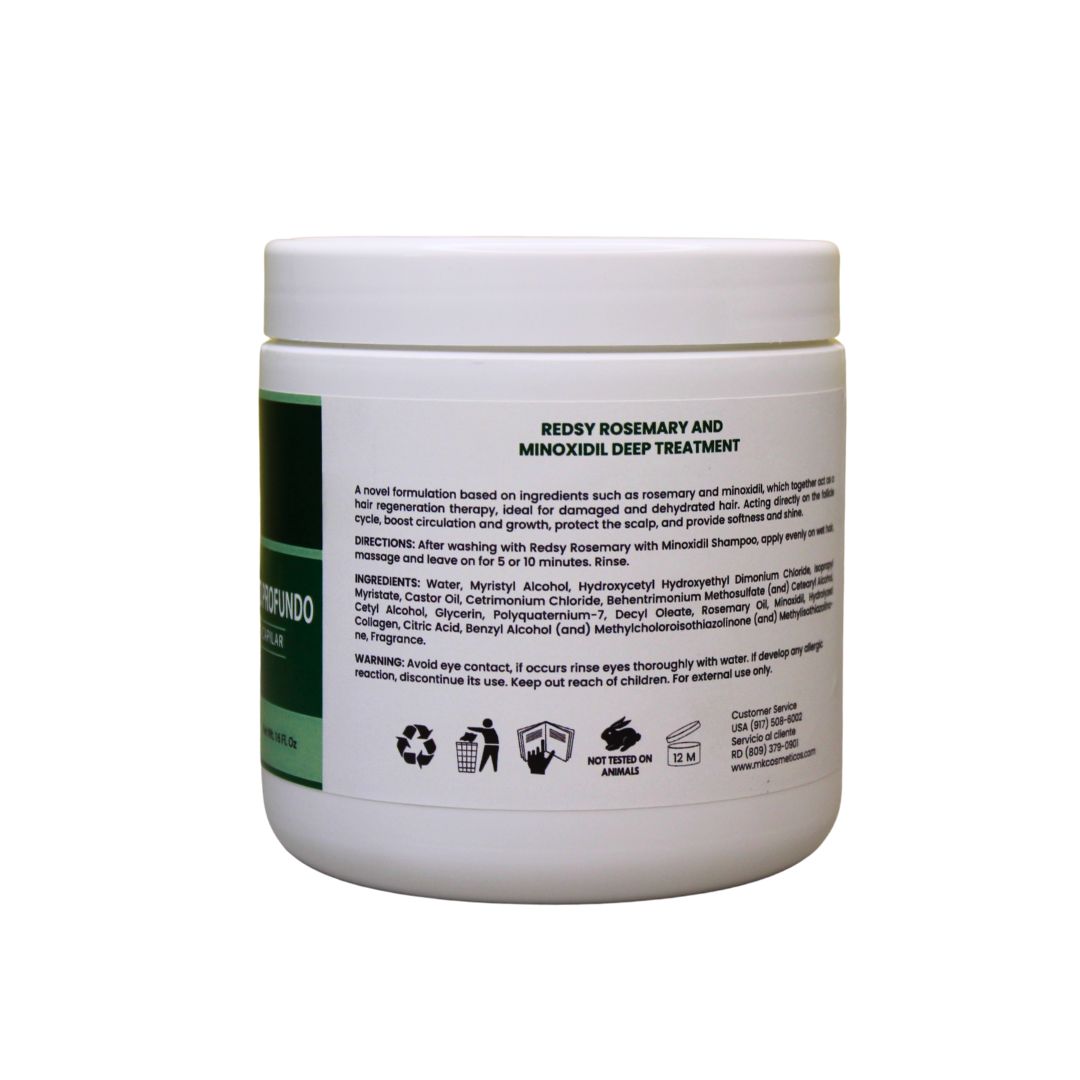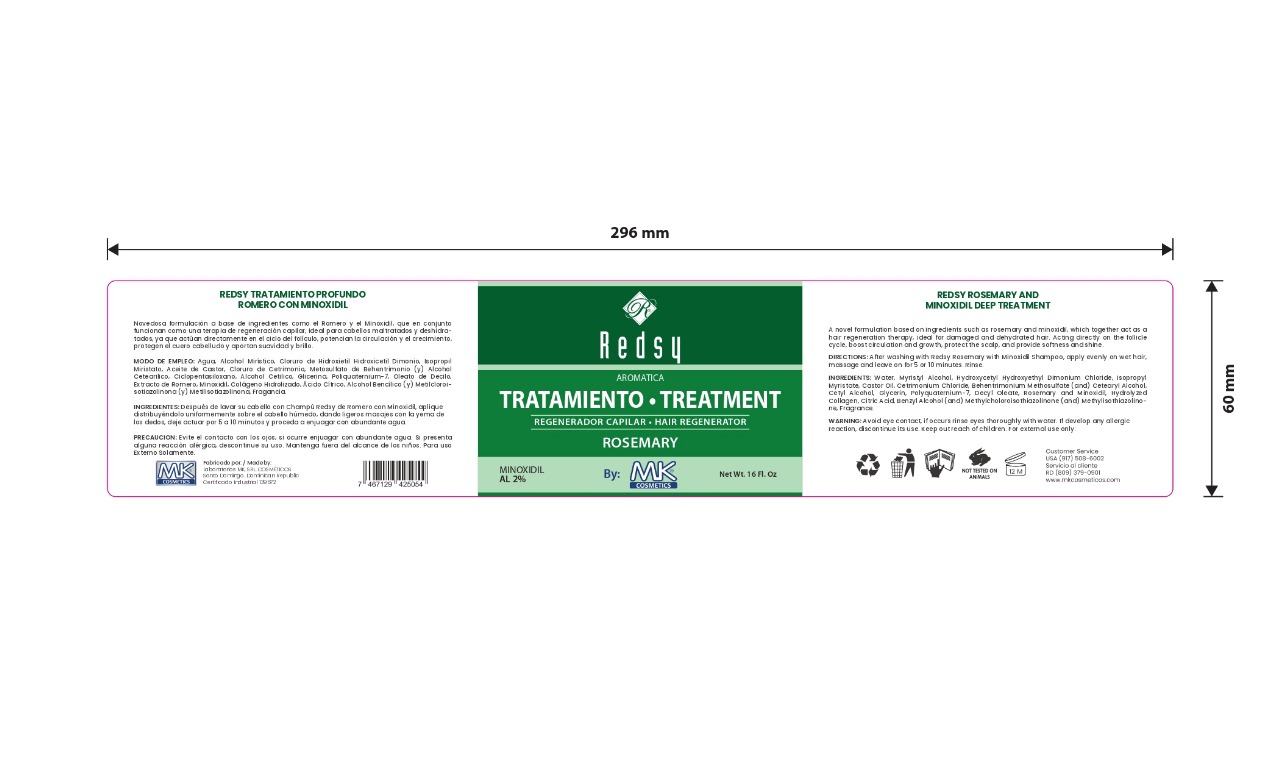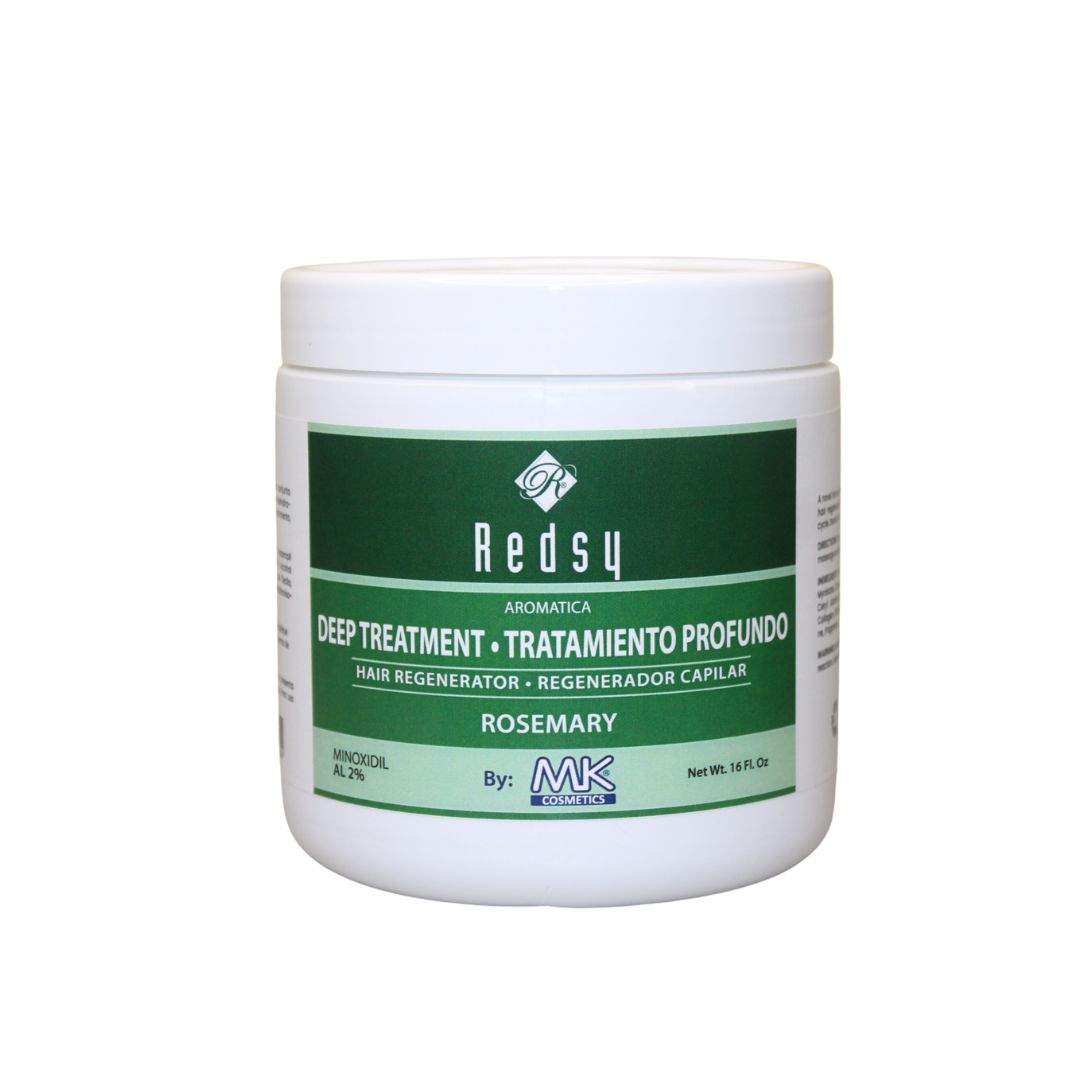 DRUG LABEL: aromatica hair tratamiento romero con minoxidil
NDC: 87022-013 | Form: CREAM
Manufacturer: LABORATORIO MK SRL
Category: otc | Type: HUMAN OTC DRUG LABEL
Date: 20251001

ACTIVE INGREDIENTS: MINOXIDIL 2 mg/456 g
INACTIVE INGREDIENTS: MYRISTYL ALCOHOL; HYDROXYCETYL HYDROXYETHYL DIMONIUM CHLORIDE; ISOPROPYL MYRISTATE; DECYL OLEATE; HYDROLYZED PORCINE COLLAGEN (ENZYMATIC; 3000 MW); CETYL ALCOHOL; BEHENTRIMONIUM METHOSULFATE; GLYCERIN; CETEARYL ALCOHOL; CITRIC ACID; BENZYL ALCOHOL; CASTOR OIL; CETRIMONIUM CHLORIDE; METHYLISOTHIAZOLINONE; METHYLCHLOROISOTHIAZOLINONE; WATER; POLYQUATERNIUM-7; ROSEMARY OIL

INDICATIONS AND USAGE

After washing with Redsy Rosemary with Minoxidil Shampoo, apply evenly on wet hair, massage and leave on for 5 or 10 minutes. Rinse.

INACTIVE INGREDIENT

Water, Myristyl Alcohol, Hydroxycetyl Hydroxyethyl Dimonium Chloride, Isopropyl Myristate, Castor Oil, Cetrimonium Chloride, Behentrimonium Methosulfate (and) Cetearyl Alcohol, Cetyl Alcohol, Glycerin, Polyquaternium-7, Decyl Oleate, Rosemary, Hydrolyzed Collagen, Citric Acid, Benzyl Alcohol (and) Methylcholoroisothiazolinone (and) Methylisothiazolinone, Fragrance.

WARNINGS

Avoid eye contact, if occurs rinse eyes thoroughly with water. If develop any allergic reaction, discontinue its use.

INFORMATION FOR OWNERS/CAREGIVERS

Customer Service USA (917)508-6002

Customer Service RD (809)379-0900

www.mkcosmeticos.com

DOSAGE AND ADMINISTRATION

After washing with Redsy Rosemary with Minoxidil Shampoo, apply evenly on wet hair, massage and leave on for 5 or 10 minutes. Rinse.

KEEP OUT OF REACH OF CHILDREN

Keep out reach of children. For external use only.

PURPOSE

Aromatica hair regenerator

PACKAGE LABEL

aromatica treatment hair regenerator rosemary with minoxidil